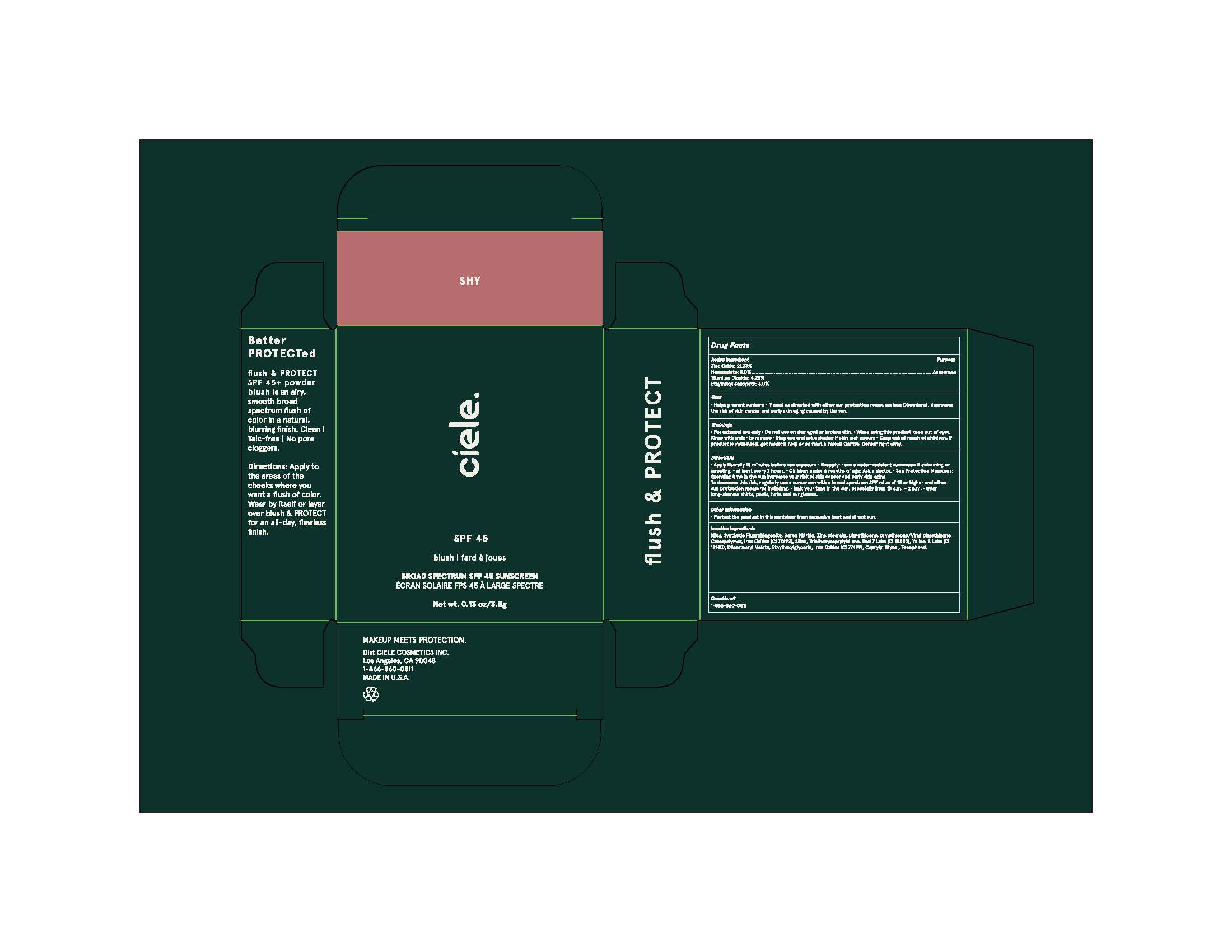 DRUG LABEL: Ciele SPF 45 flush PROTECT
NDC: 83103-1001 | Form: POWDER
Manufacturer: LÚE COSMETICS INC
Category: otc | Type: HUMAN OTC DRUG LABEL
Date: 20251204

ACTIVE INGREDIENTS: HOMOSALATE 5 mg/100 mg; ETHYLHEXYL SALICYLATE 3 mg/100 mg; ZINC OXIDE 21.372 mg/100 mg; TITANIUM DIOXIDE 4.25 mg/100 mg
INACTIVE INGREDIENTS: MICA; BORON NITRIDE; ZINC STEARATE; DIMETHICONE; DIMETHICONE/VINYL DIMETHICONE CROSSPOLYMER (SOFT PARTICLE); SILICON DIOXIDE; TRIETHOXYCAPRYLYLSILANE; RED 7; DIISOSTEARYL MALATE; ETHYLHEXYLGLYCERIN; YELLOW 5; ULTRAMARINE VIOLET; SILICON; CAPRYLYL GLYCOL; TOCOPHEROL; BROWN IRON OXIDE

DRUG FACTS

Active Ingredients

Zinc Oxide 21.37%

Homosalate 5.0%

Titanium Dioxide 4.25%

Ethylhexyl Salicylate 3.0%

Uses

● helps prevent sunburn
● if used as directed with other sun protection measures (see Directions),
decreases the risk of skin cancer and early skin aging caused by the sun

Warnings

For external use only
Do not use on damaged or broken skin.
When using this product keep out of eyes. Rinse with water to remove.
Stop use and ask a docor if rash occurs
Keep out of reach of children. If swallowed, get medical help or contact a Poison Control Center right away.

Directions

• apply liberally15 minutes before sun exposure and as needed
• reapply at least every 2 hours.

• use a water resistant sunscreen if swimming or sweating
• Sun Protection Measures. Spending time in the sun

increases your risk of skin cancer and early skin aging. To decrease
this risk, regularly use a sunscreen with a Broad Spectrum SPF
value of 15 or higher and other sun protection measures including:
• limit time in the sun, especially from 10 a.m. - 2 p.m.
• wear long-sleeved shirts, pants, hats, and sunglasses
• children under 6 months of age: Ask a doctor

Inactive ingredients

Synthetic Fluorphlogopite, Mica, Boron Nitride, Zinc Stearate, Dimethicone, Dimethicone/Vinyl Dimethicone Crosspolymer, Silica, Triethoxycaprylylsilane, Diisostearyl Malate, Ethylhexylglycerin, Caprylyl Glycol, Tocopherol, Red 7 Lake (CI 15850), Iron Oxides (CI 77492), Iron Oxides (CI 77499), Yellow 5 Lake (CI 19140), Ultramarines (CI 77007)

Other Information

Protect the product in this container from excessive heat and direct sun.

Questions?

1-866-860-0811

Purpose

Sunscreen

Keep out of reach of children